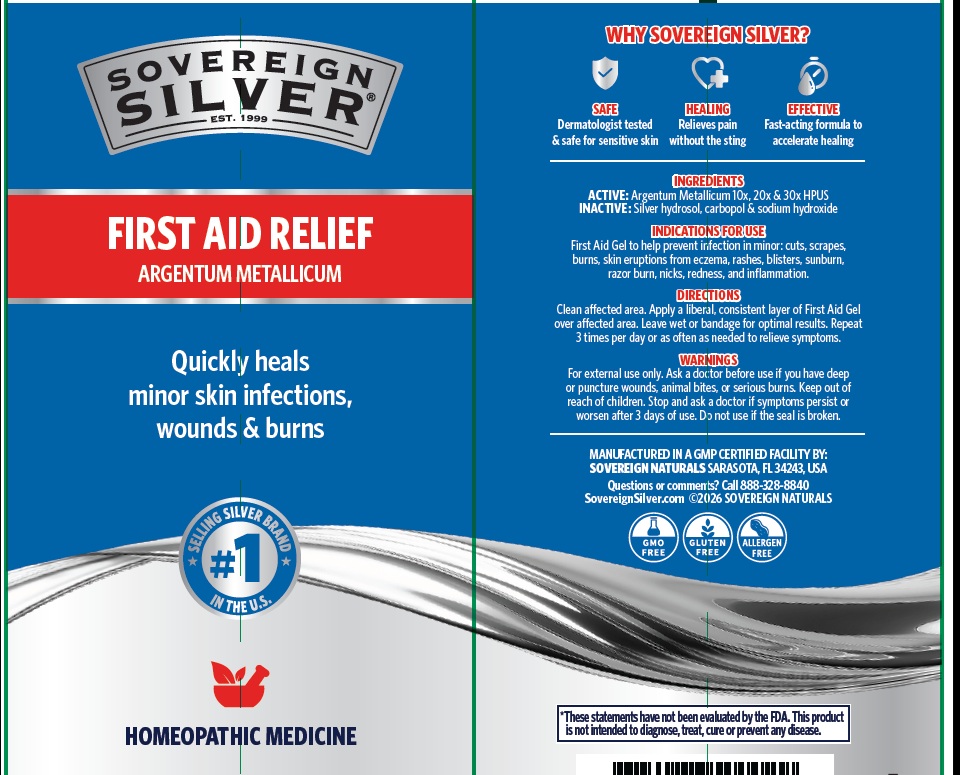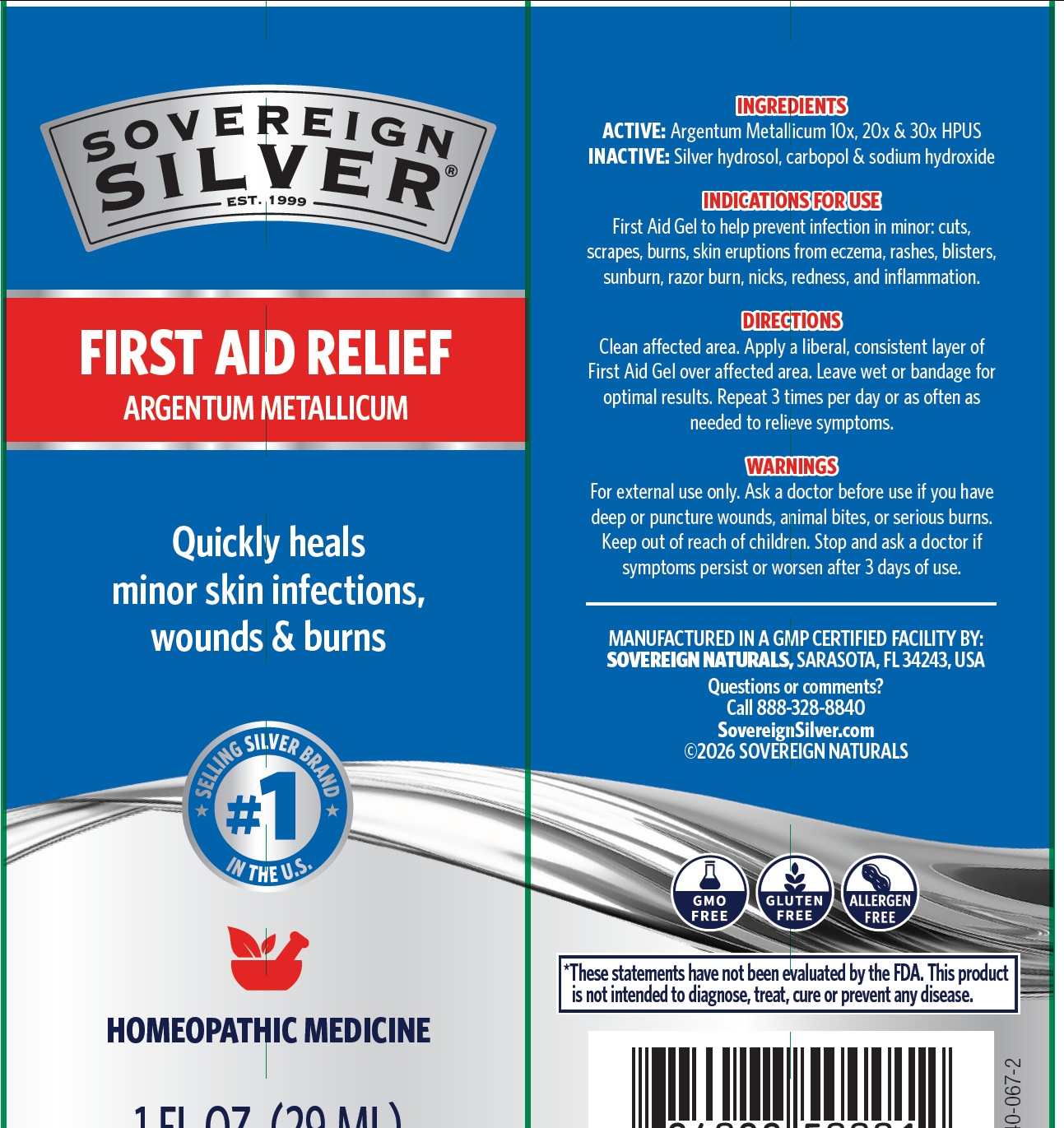 DRUG LABEL: SOVEREIGN SILVER NATURAL HEALING SKIN CARE
NDC: 52166-025 | Form: GEL
Manufacturer: Natural Immunogenics Corp.dba SOVEREIGN NATURALS
Category: homeopathic | Type: HUMAN OTC DRUG LABEL
Date: 20251124

ACTIVE INGREDIENTS: SILVER 30 [hp_X]/1 mL
INACTIVE INGREDIENTS: CARBOMER HOMOPOLYMER, UNSPECIFIED TYPE; SODIUM HYDROXIDE

Active Ingredient

ARGENTUM METALLICUM 10X, 20X, 30X

Purpose

TOPICAL ANALGESIC

Uses

FOR RELIEF OF SYMPTOMS DUE TO SKIN ERUPTIONS FROM ACNE, ECZEMA, MINOR INFECTION, RASHES, BLISTERS, SUNBURN, RAZOR BURN, MINOR NICKS & CUTS, REDNESS & MINOR INFLAMMATION

Warnings

FOR EXTERNAL USE ONLY. ASK A DOCTOR BEFORE SE IF YOU HAVE DEEP OR PUNCTURE WOUNDS, ANIMAL BITES OR SERIOUS BURNS. KEEP OUT OF REACH OF CHILDREN. STOP AND ASK A DOCTOR IF SYMPTOMS PERSIST OR WORSEN AFTER 3 DAYS OF USE. DO NOT USE IF THE SEAL IS BROKEN.

Directions

GENTLY CLEAN AFFECTED AREA. APPLY A LIBERAL, CONSISTENT LAYER OF SKIN CARE GEL OVER AFFECTED AREA. REPEAT 3 TIMES PER DAY OR AS OFTEN AS NEEDED TO RELIEVE SYMPTOMS. SAFE ON SENSITIVE SKIN.

Inactive Ingredients

CARBOPOL, SODIUM HYDROXIDE